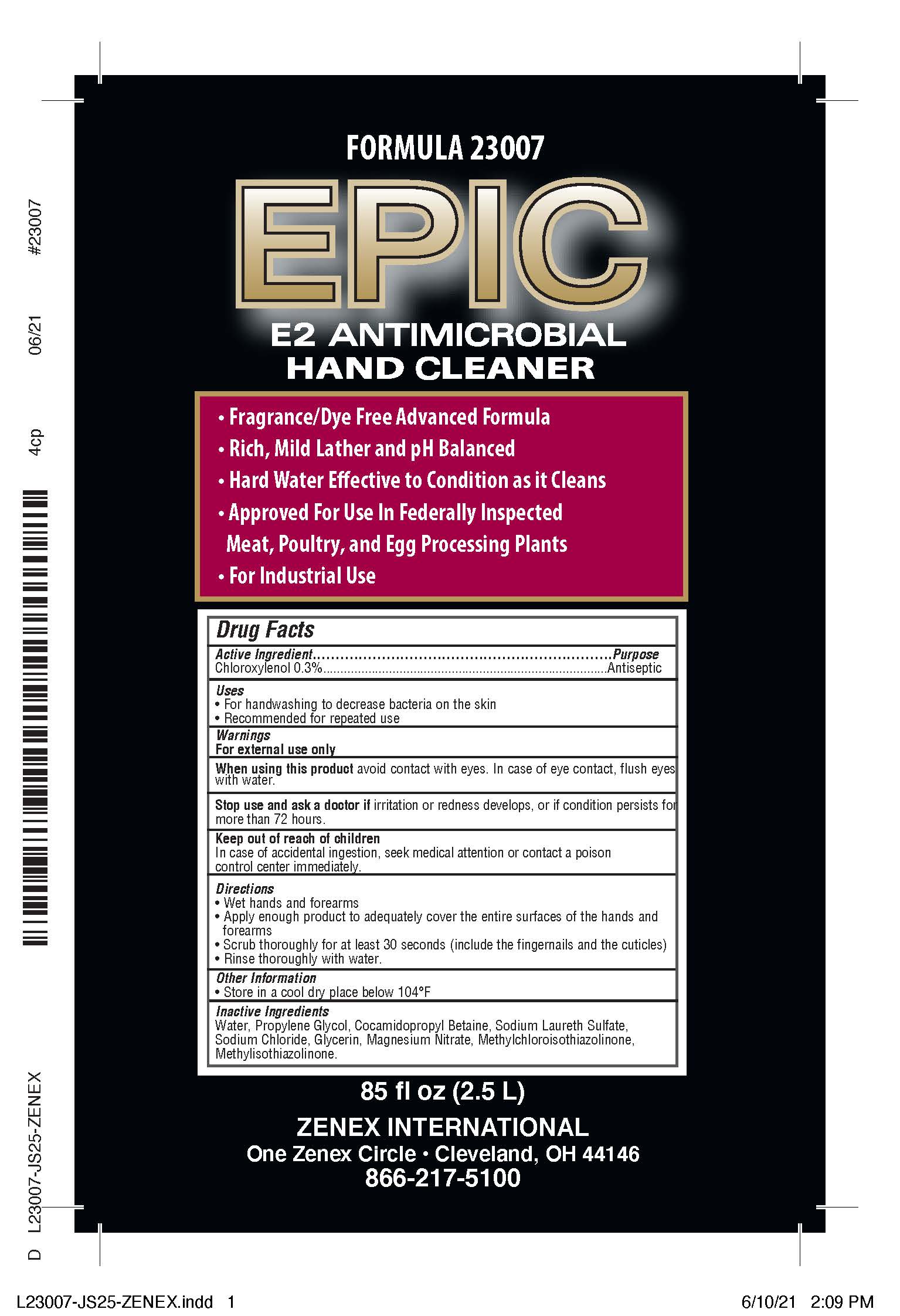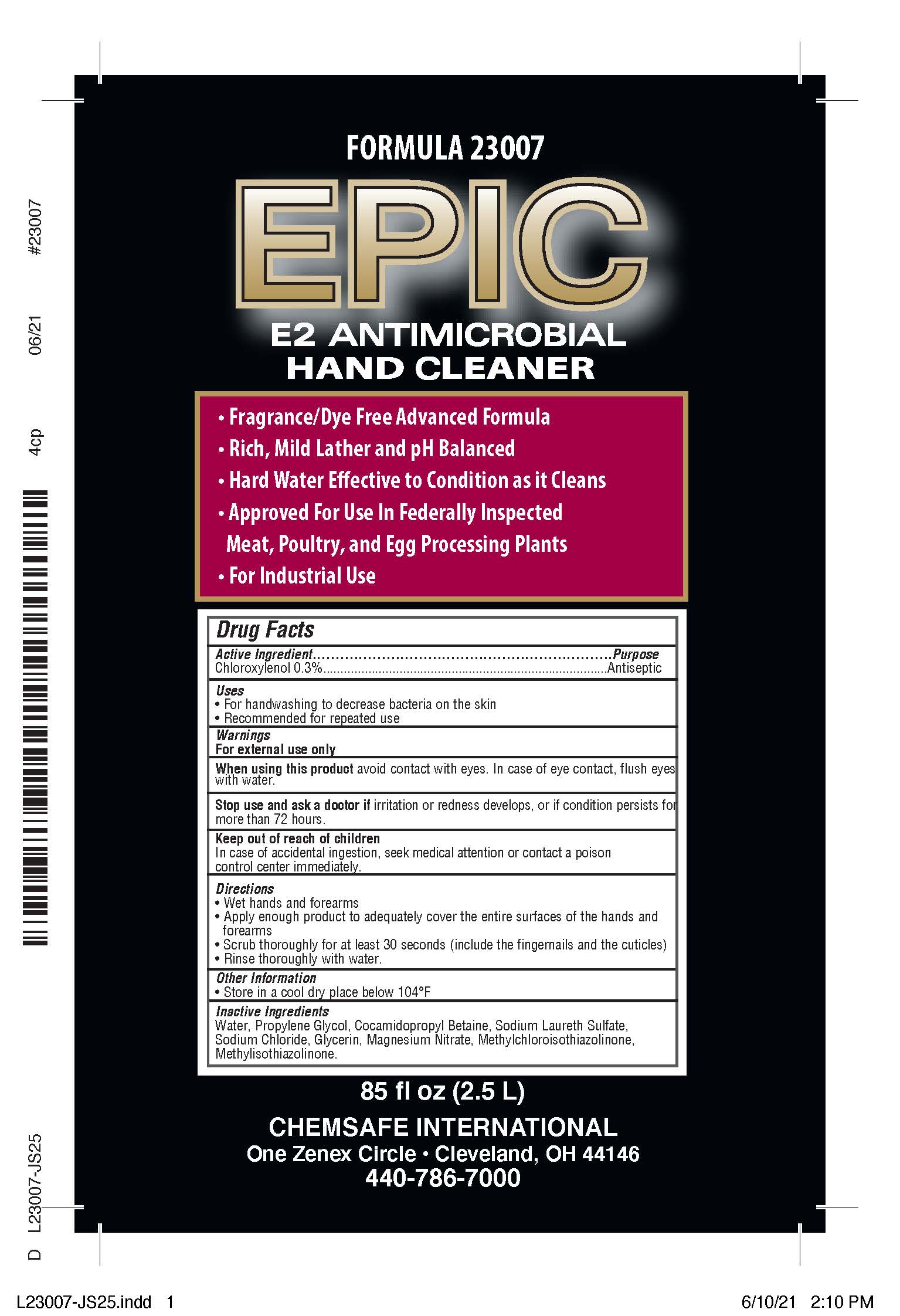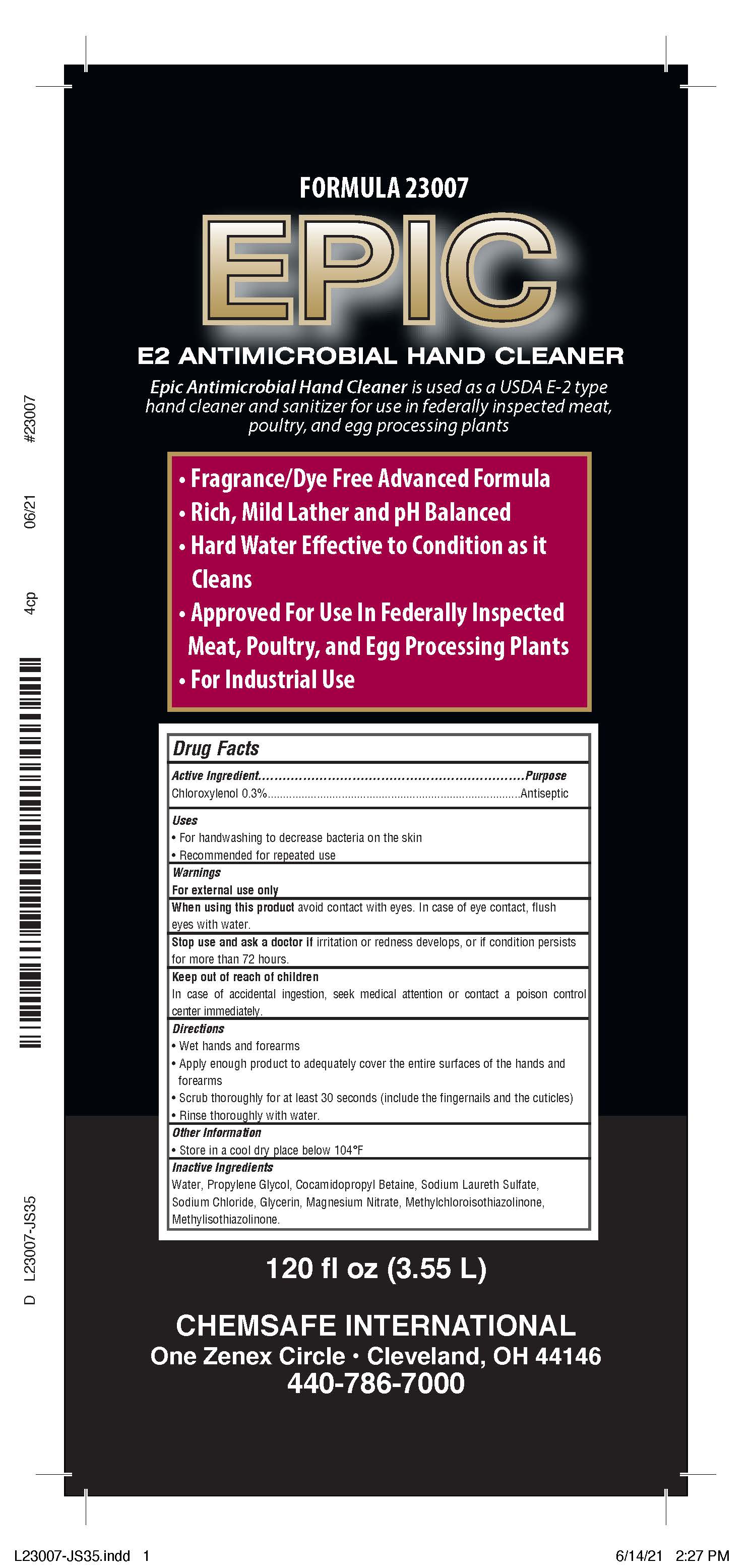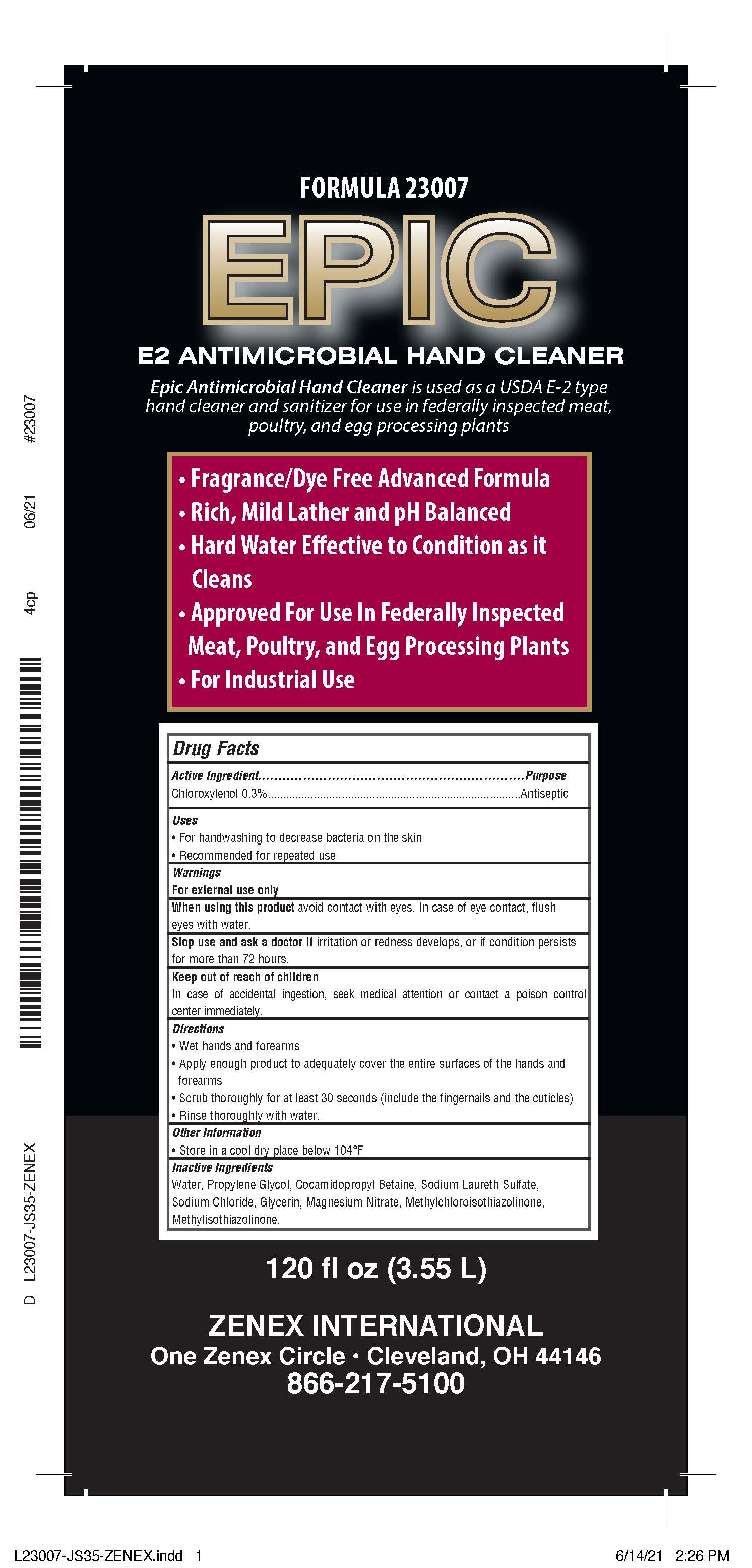 DRUG LABEL: EPIC
NDC: 74146-237 | Form: SOAP
Manufacturer: GM Industrial, Inc.
Category: otc | Type: HUMAN OTC DRUG LABEL
Date: 20210609

ACTIVE INGREDIENTS: CHLOROXYLENOL 3 mg/1 mL
INACTIVE INGREDIENTS: METHYLCHLOROISOTHIAZOLINONE; COCAMIDOPROPYL BETAINE; MAGNESIUM NITRATE; GLYCERIN; SODIUM LAURETH SULFATE; METHYLISOTHIAZOLINONE; SODIUM CHLORIDE; PROPYLENE GLYCOL; WATER

BOXED WARNING

ACTIVE INGREDIENT

Chloroxylenol 0.3%

PURPOSE

Antiseptic

Uses

- For handwashing to decrease bacteria on the skin
- Recommended for repeated use

Warnings

For external use only

When using this product avoid contact with eyes. In case of eye contact, flush eyes with water.

Stop use and ask a doctor if irritation or redness develops, or if condition persists for more than 72 hours.

Keep out of reach of children

In case of accidental ingestion, seek medical attention or contact a poison control center immediately.

Directions

- Wet hands and forearms
- Apply enough product to adequately cover the entire surfaces of the hands and forearms
- Scrub thoroughly for at least 30 seconds (include the fingernails and the cuticles)
- Rinse thoroughly with water.

Other Information

- Store in a cool dry place below 104°F

Inactive Ingredients

Water, Propylene Glycol, Cocamidopropyl Betaine, Sodium Laureth Sulfate, Sodium Chloride, Glycerin, Magnesium Nitrate, Methylchloroisothiazolinone, Methylisothiazolinone.

2.5 L PDP CHEM EPIC

2.5 L pdp 74146-237-79

2.5 L PDP ZENEX EPIC

2.5 L pdp 74146-237-77

3.5 L PDP CHEM EPIC

3.5 L 74146-237-75

3.5 L PDP ZENEX EPIC

3.55 L 74146-237-73